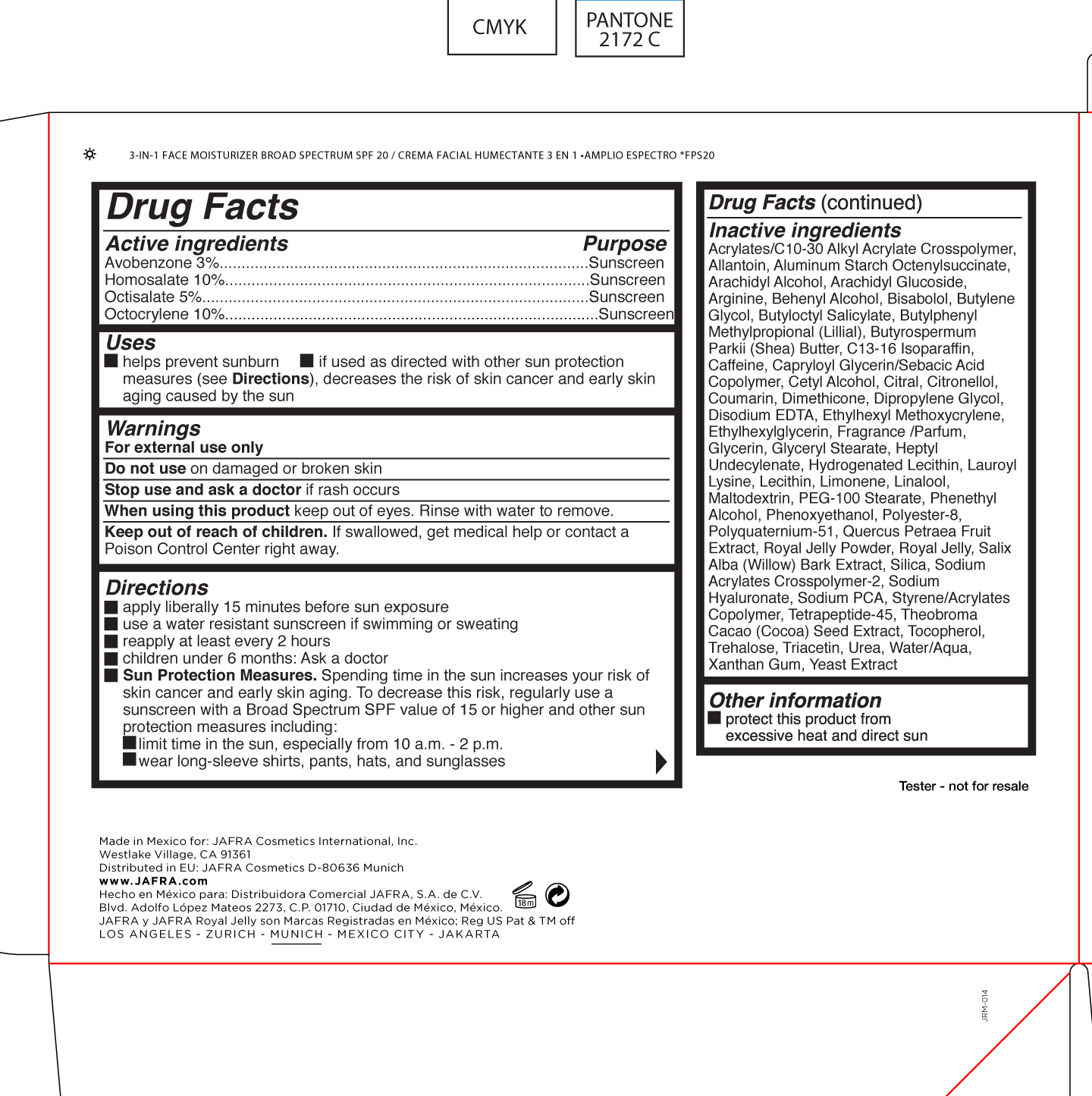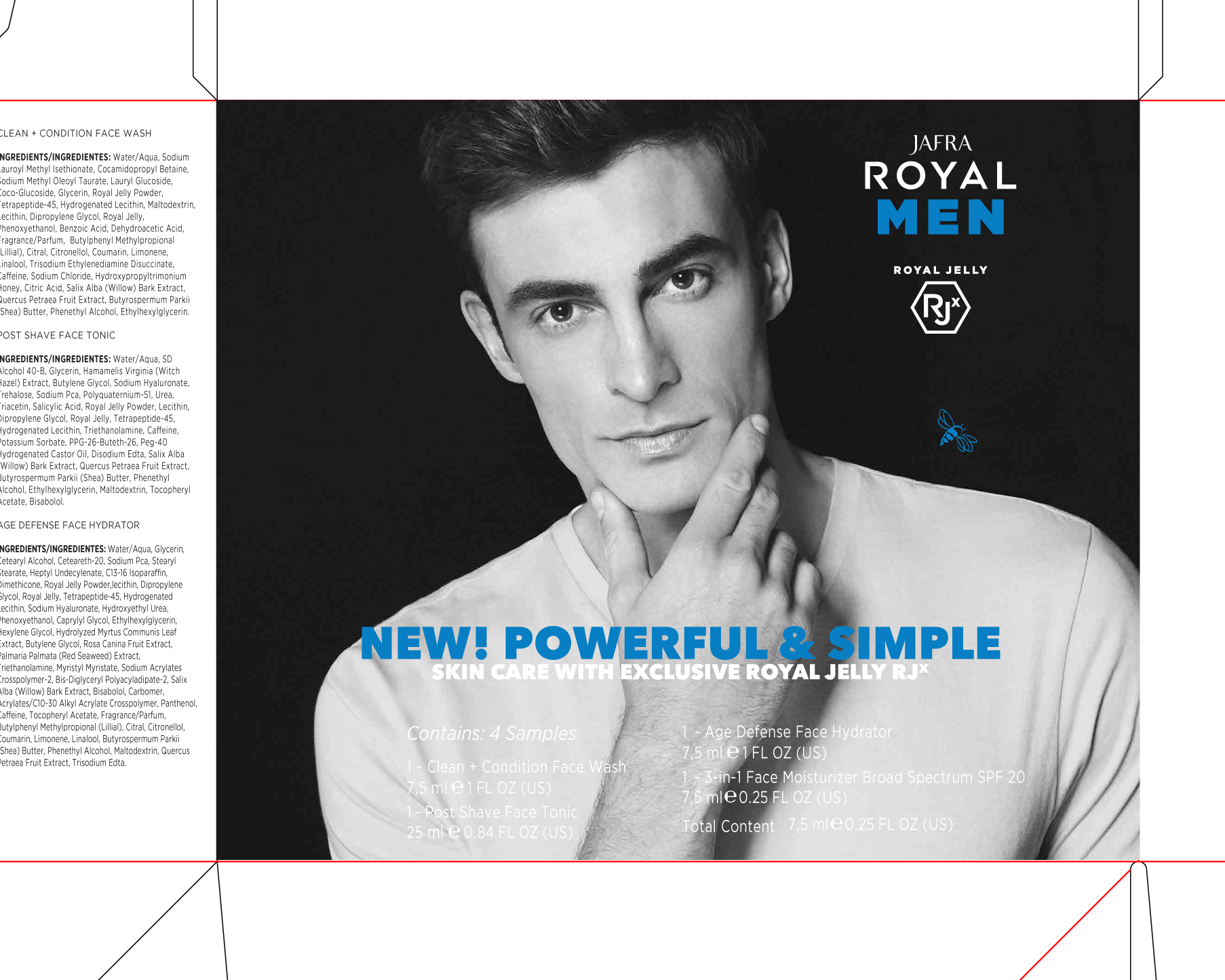 DRUG LABEL: Jafra Royal Men Sample Set
NDC: 68828-395 | Form: KIT | Route: TOPICAL
Manufacturer: Jafra International Cosmetics
Category: otc | Type: HUMAN OTC DRUG LABEL
Date: 20190408

ACTIVE INGREDIENTS: HOMOSALATE 10 g/100 mL; OCTOCRYLENE 10 g/100 mL; AVOBENZONE 3 g/100 mL; OCTISALATE 5 g/100 mL
INACTIVE INGREDIENTS: ARACHIDYL GLUCOSIDE; LEVOMENOL; C13-16 ISOPARAFFIN; CAFFEINE; GLYCERIN; ETHYLHEXYL METHOXYCRYLENE; SODIUM PYRROLIDONE CARBOXYLATE; TRIACETIN; UREA; WATER; YEAST, UNSPECIFIED; PEG-100 STEARATE; TREHALOSE; TOCOPHEROL; XANTHAN GUM; SILICON DIOXIDE; COCOA; MALTODEXTRIN; PHENOXYETHANOL; SALIX ALBA BARK; HYALURONATE SODIUM; BUTYLENE GLYCOL; BUTYLOCTYL SALICYLATE; GLYCERYL MONOSTEARATE; HEPTYL UNDECYLENATE; ALUMINUM STARCH OCTENYLSUCCINATE; ARACHIDYL ALCOHOL; ARGININE; DOCOSANOL; CITRAL; .BETA.-CITRONELLOL, (R)-; COUMARIN; EDETATE DISODIUM ANHYDROUS; CAPRYLOYL GLYCERIN/SEBACIC ACID COPOLYMER (2000 MPA.S); CETYL ALCOHOL; DIMETHICONE; CARBOMER COPOLYMER TYPE A (ALLYL PENTAERYTHRITOL CROSSLINKED); ALLANTOIN; BUTYLPHENYL METHYLPROPIONAL; SHEA BUTTER; DIPROPYLENE GLYCOL; ETHYLHEXYLGLYCERIN; LIMONENE, (+)-; LINALOOL, (+/-)-; PHENYLETHYL ALCOHOL; POLYQUATERNIUM-51 (2-METHACRYLOYLOXYETHYL PHOSPHORYLCHOLINE/N-BUTYL METHACRYLATE; 3:7); LAUROYL LYSINE; LECITHIN, SOYBEAN; POLYESTER-8 (1400 MW, CYANODIPHENYLPROPENOYL CAPPED); HYDROGENATED SOYBEAN LECITHIN

Jafra Royal Men Royal Jelly Sample set

Active Ingredients Purpose

Avobenzone 3% Sunscreen

Homosalate 10% Sunscreen

Octisalate 5% Sunscreen

Octocrylene 10% Sunscreen

Uses

- Helps Prevent Sunburn
- If used as directed with other sun protection measures (see Directions), decreases the risk of skin cancer and early skin aging caused by the sun

KEEP OUT OF REACH OF CHILDREN

Keep out reach of children. If swallowed, get medical help or contact a Poison Control Center right away.

Stop use and ask a doctor if rash occurs

Warnings

Do not use on damaged or broken skin

Whe using this product keep out of eyes. RInse with water to remove.

Directions

- Apply liberally 15 minutes before sun exposure
- Reapply: after 80 minutes of swimming or sweating
- Immediately after towel drying
- At least every 2 hours
- Children under 6 months: Ask a doctor

Sun Protection Measures. Spending time in the sun increases your risk of skin cancer and early skin aging. To decrease this risk, regularly use a sunscreen with a Broad Spectrum SPF value 15 or higher and other sun protection measures including:
Limit time in the sun, especially from 10a.m. – 2p.m.
Wear long-sleeve shirts, pants, hats, and sunglasses

INACTIVE INGREDIENT

INGREDIENTS/INGREDIENTES: Water/Aqua, Glycerin, Cetearyl Alcohol, Ceteareth-20, Sodium Pca, Stearyl Stearate, Heptyl Undecylenate, C13-16 Isoparaffin, Dimethicone, Royal Jelly Powder, lecithin, Dipropylene Glycol, Royal Jelly, Tetrapeptide-45, Hydrogenated Lecithin, Sodium Hyaluronate, Hydroxyethyl Urea, Phenoxyethanol, Caprylyl Glycol, Ethylhexylglycerin,
Hexylene Glycol, Hydrolyzed Myrtus Communis Leaf Extract, Butylene Glycol, Rosa Canina Fruit Extract,
Palmaria Palmata (Red Seaweed) Extract, Triethanolamine, Myristyl Myristate, Sodium Acrylates Crosspolymer-2, Bis-Diglyceryl Polyacyladipate-2, Salix Alba (Willow) Bark Extract, Bisabolol, Carbomer, Acrylates/C10-30 Alkyl Acrylate Crosspolymer, Panthenol, Caffeine, Tocopheryl Acetate, Fragrance/Parfum, Butylphenyl Methylpropional (Lillial), Citral, Citronellol, Coumarin, Limonene, Linalool, Butyrospermum Parkii (Shea) Butter, Phenethyl Alcohol, Maltodextrin, Quercus Petraea Fruit Extract, Trisodium Edta.

PACKAGE LABEL

Jafra Royal Men

Contains 4 samples

3-in-1 Face Moisturizer Broad Spectrum SPF 20

7.5 ml 0.25 FL OZ

Clean + Condition Face Wash

7.5ml 1 FL OZ

Post Shave Face Tonic

25 ml 0.84 FL OZ

Age Defense Face Hydrator

7.5 ml 1 FL OZ